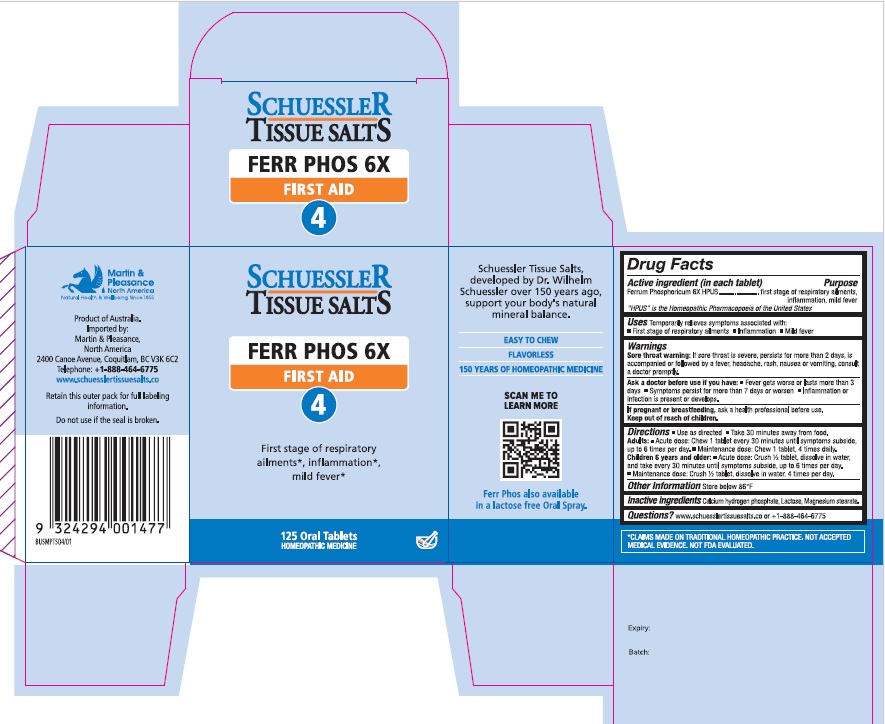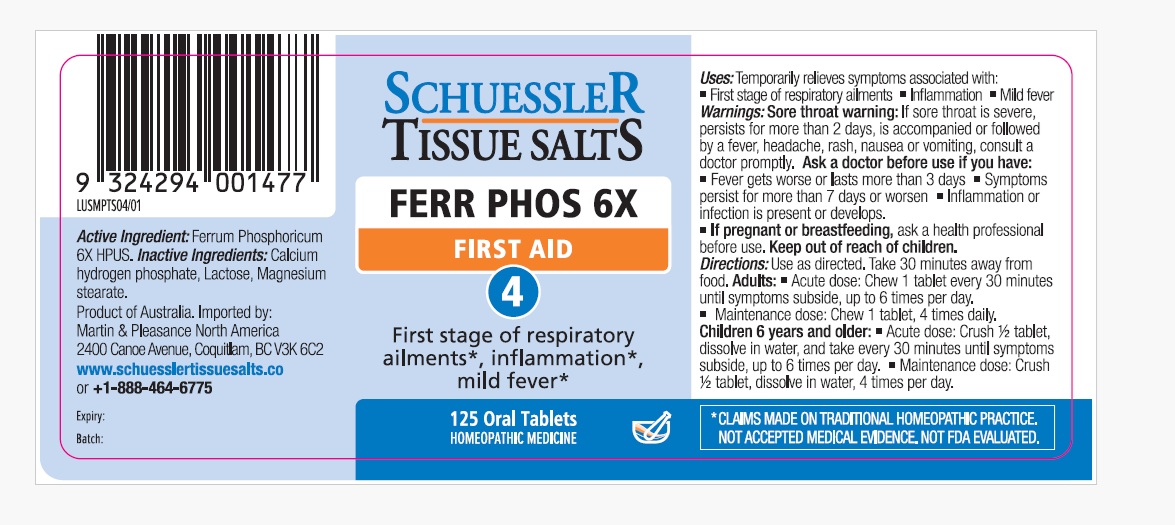 DRUG LABEL: Schuessler Tissue Salts Ferr Phos First Aid 4
NDC: 84999-016 | Form: TABLET, CHEWABLE
Manufacturer: Martin & Pleasance Pty Ltd
Category: homeopathic | Type: HUMAN OTC DRUG LABEL
Date: 20250718

ACTIVE INGREDIENTS: FERROUS PHOSPHATE 6 [hp_X]/1 1
INACTIVE INGREDIENTS: MAGNESIUM STEARATE; LACTOSE MONOHYDRATE; ANHYDROUS DIBASIC CALCIUM PHOSPHATE

Active Ingredients Purpose

Ferrum Phosphoricum 6X HPUS first stage of respiratory ailments, inflammation, mild fever

" HPUS" is the Homeopathic Pharmacopoeia of the United States

Uses

Temporarily relieves symptoms associated with

- first stage of respiratory ailments
- inflammation
- mild fever

Warnings

Sore throat warning:If sore throat is severe, persists more than 2 days is accompanied or followed by a fever, headche, rash, nausea or vomiting, consult a doctor promptly.

Ask a doctor before use if you have

- Fever gets worse or lasts more than 3 days.
- Symptoms persists for more than 7 days or worsen
- Inflammation or infection is present or develops

If pregnant or breastfeeding, ask a health professional before use. Keep out of reach of children.

Directions

- Use as directed
- Take 30 minutes away from food

Adults: Acute dose: Chew 1 tablet every 30 minutes until symptoms subside up to 6 times per day.

Maintenance dose: Chew 1 tablet, 4 times daily.

Children 6 years and older: Acute dose: Crush 1/2 tablet, dissolve in water, and take every 30 minutes until symptoms subside, up to six times per day.

Maintenance dose :Crush 1/2 tablet, dissolve in water, 4 times per day.

Other Information

Store below 86°F

Inactive Ingredients

Calcium hydrogen phosphate, Lactose, Magnesium stearate

Questions?www.schuesslertissuesalts.co or + 1-888-464-6775